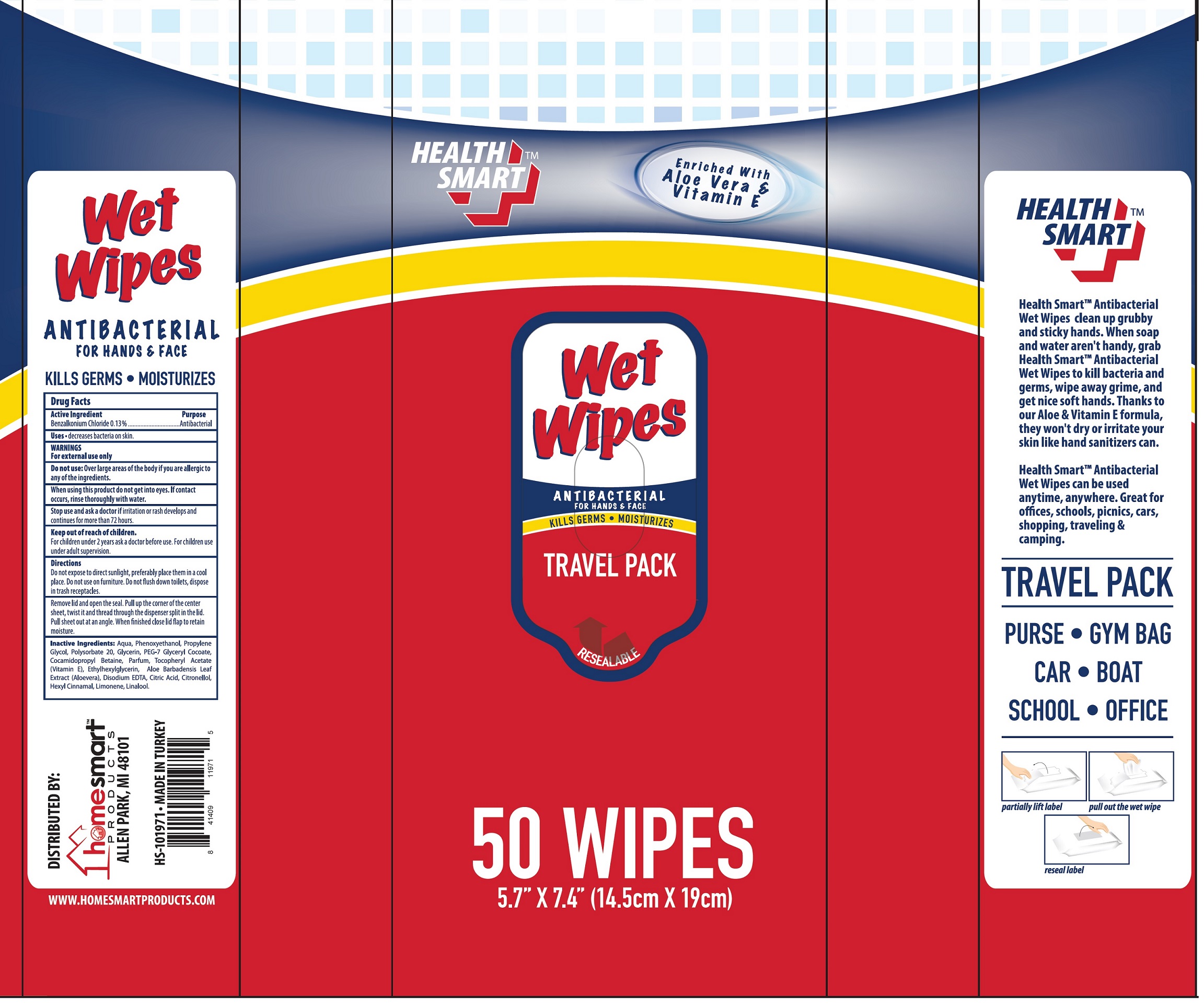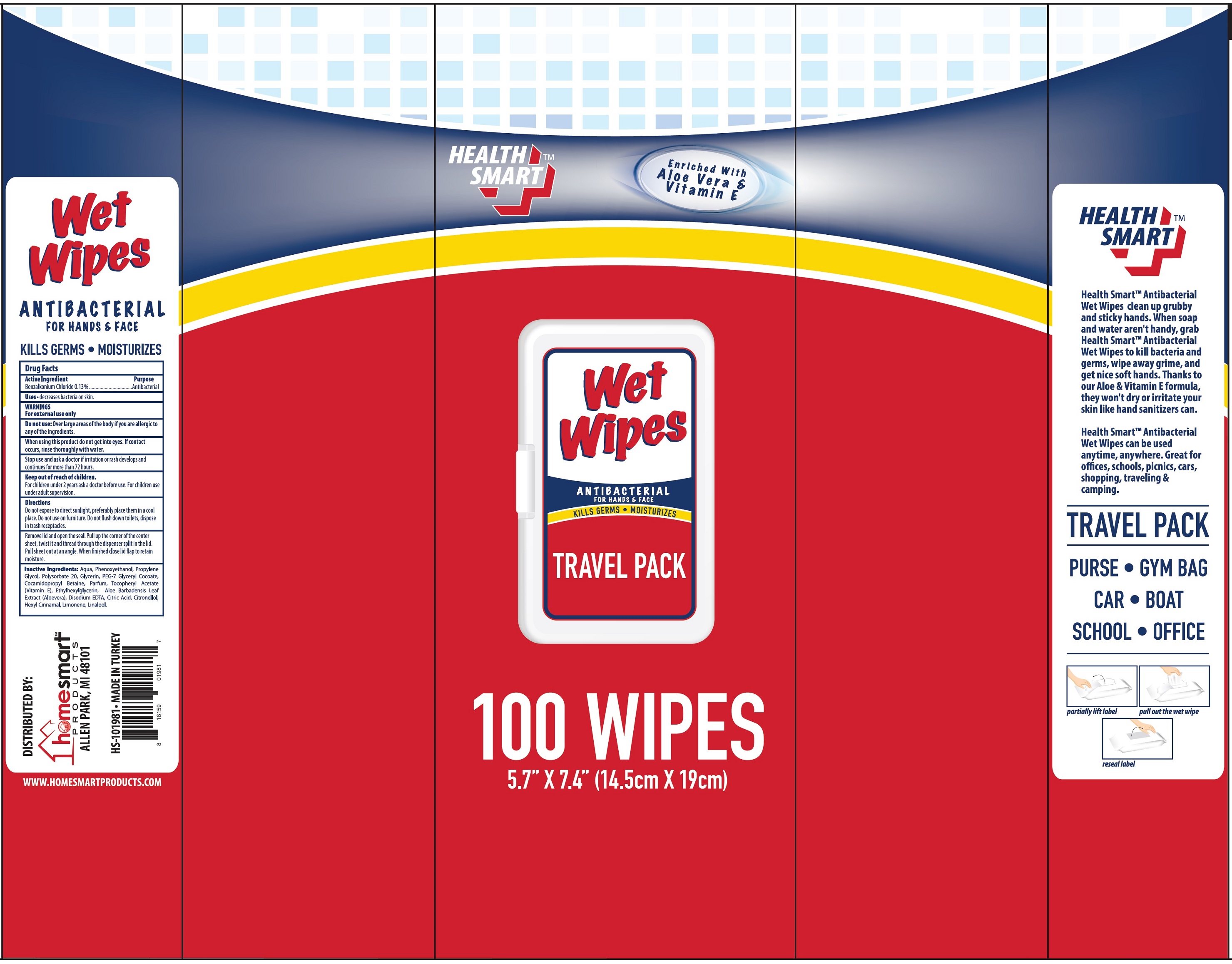 DRUG LABEL: Health Smart Antibacterial Wet Wipes
NDC: 52862-613 | Form: CLOTH
Manufacturer: International Wholesale, Inc.
Category: otc | Type: HUMAN OTC DRUG LABEL
Date: 20231116

ACTIVE INGREDIENTS: BENZALKONIUM CHLORIDE 1.3 mg/1 g
INACTIVE INGREDIENTS: WATER; PHENOXYETHANOL; PROPYLENE GLYCOL; POLYSORBATE 20; GLYCERIN; PEG-7 GLYCERYL COCOATE; COCAMIDOPROPYL BETAINE; .ALPHA.-TOCOPHEROL ACETATE; ETHYLHEXYLGLYCERIN; ALOE VERA LEAF; EDETATE DISODIUM ANHYDROUS; CITRIC ACID MONOHYDRATE; .BETA.-CITRONELLOL, (R)-; .ALPHA.-HEXYLCINNAMALDEHYDE; LIMONENE, (+)-; LINALOOL, (+/-)-

Health Smart Antibacterial Wet Wipes

Active Ingredient

Benzalkonium Chloride 0.13%

Purpose

Antibacterial

Uses

- decreases bacteria on skin.

WARNINGS

For external use only

Do not use:

Over large areas of the body if you are allergic to any of the ingredients.

When using this product

do not get into eyes. If contact occurs, rinse thoroughly with water.

Stop use and ask a doctor

if irritation or rash develops and continues for more than 72 hours.

Keep out of reach of children.

For children under 2 years ask a doctor before use. For children use under adult supervision.

Directions

Do not expose to direct sunlight, preferably place them in a cool place. Do not use on furniture. Do not flush down toilets, dispose in trash receptacles.

Remove lid and open the seal. Pull up the corner of the center sheet, twist it and thread through the dispenser split in the lid.Pull sheet out at an angle. When finished close lid flap to retain moisture.

Inactive Ingredients:

Aqua, Phenoxyethanol, Propylene Glycol, Polysorbate 20, Glycerin, PEG-7 Glyceryl Cocoate, Cocamidopropyl Betaine, Parfum, Tocopheryl Acetate (Vitamin E), Ethylhexylglycerin, Aloe Barbadensis Leaf Extract (Aloevera), Disodium EDTA, Citric Acid, Citronellol, Hexyl Cinnamal, Limonene, Linalool.